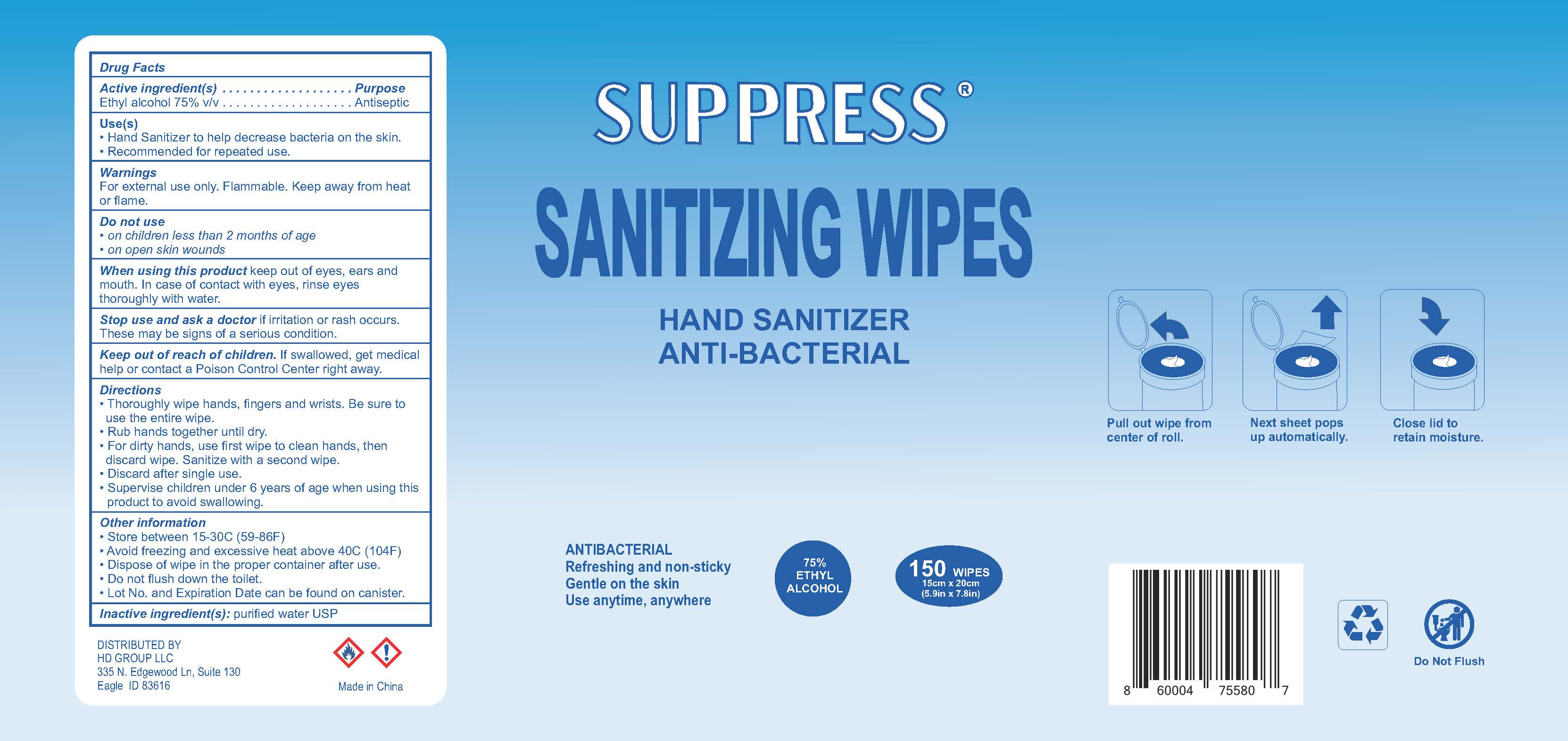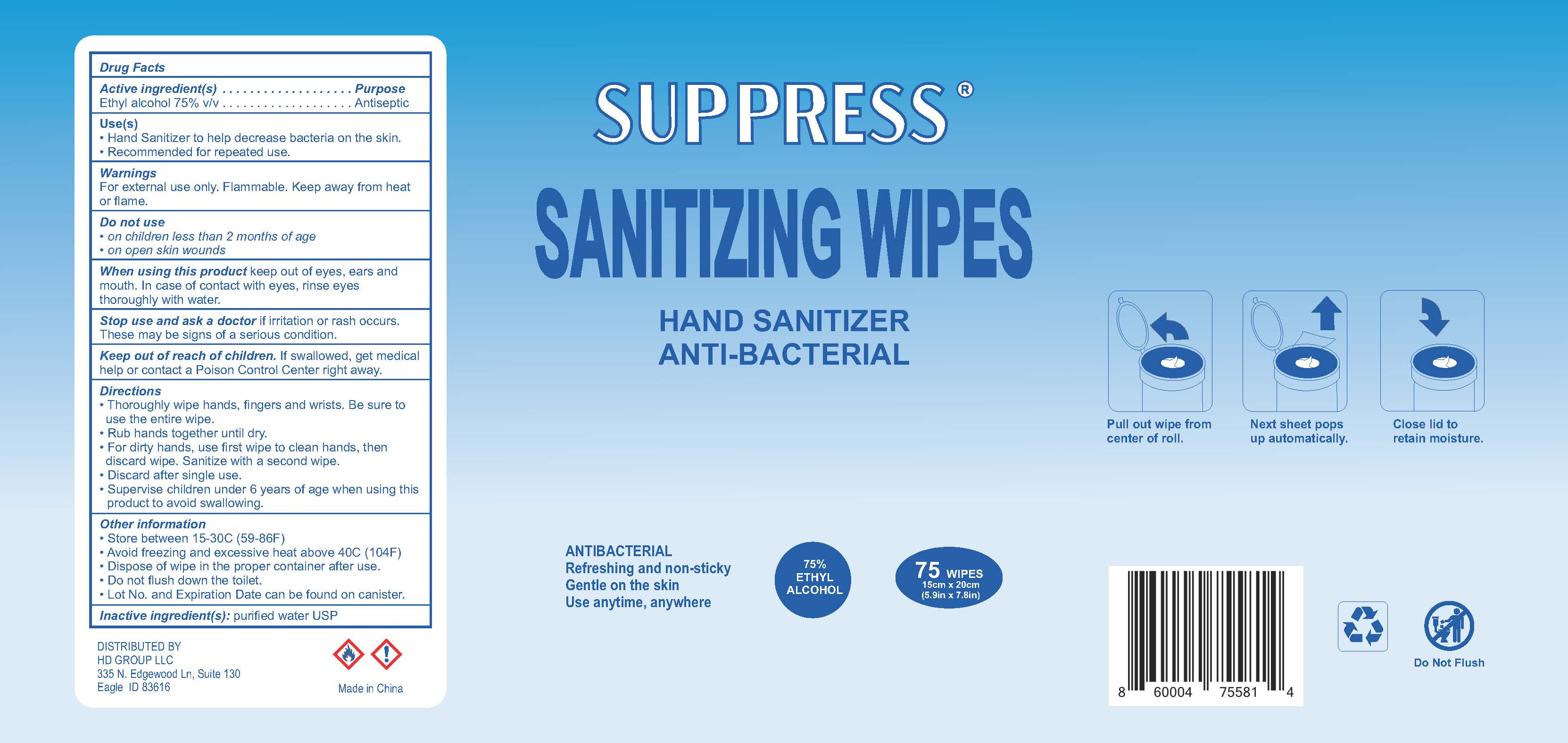 DRUG LABEL: SUPPRESS Hand Sanitizing Wipes
NDC: 77343-101 | Form: CLOTH
Manufacturer: HD Group LLC
Category: otc | Type: HUMAN OTC DRUG LABEL
Date: 20220114

ACTIVE INGREDIENTS: ALCOHOL 75 mL/100 mL
INACTIVE INGREDIENTS: WATER

SUPPRESS Hand Sanitizing Wipes

Active Ingredient(s)

Ethyl Alcohol 75% v/v

Purpose

Antiseptic

Use

- Hand Sanitizer to help decrease bacteria on the skin.
- Recommended for repeated use.

Warnings

For external use only. Flammable. Keep away from heat or flame

Do not use

- on children less than 2 months of age
- on open skin wounds

When using this product keep out of eyes, ears, and mouth. In case of contact with eyes, rinse eyes thoroughly with water.

Stop use and ask a doctor if irritation or rash occurs. These may be signs of a serious condition.

Keep out of reach of children. If swallowed, get medical help or contact a Poison Control Center right away.

Directions

- Thoroughly wipe hands, fingers and wrists. Be sure to use the entire wipe.
- Rub hands together until dry.
- For dirty hands, use first wipe to clean hands, then discard wipe. Sanitize with a second wipe.
- Discard after single use.

- Supervise children under 6 years of age when using this product to avoid swallowing.

Other information

- Store between 15-30C (59-86F)
- Avoid freezing and excessive heat above 40C (104F)
- Dispose of wipe in the proper container after use.
- Do not flush down the toilet.
- Lot No. and Expiration Date can be found on canister.

Inactive ingredients

purified water USP

Distributed By

HD Group LLC

335 N Edgewood Ln, Suite 130

Eagle, ID 83616

SUPPRESS Hand Sanitizing Wipes- 150 Wipes Label

150 Wipes

NDC: 77343-101-01

SUPPRESS Hand Sanitizing Wipes- 75 Wipes Label

75 Wipes

NDC: 77343-101-02